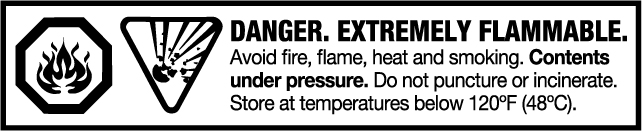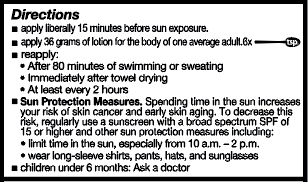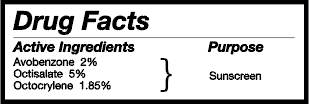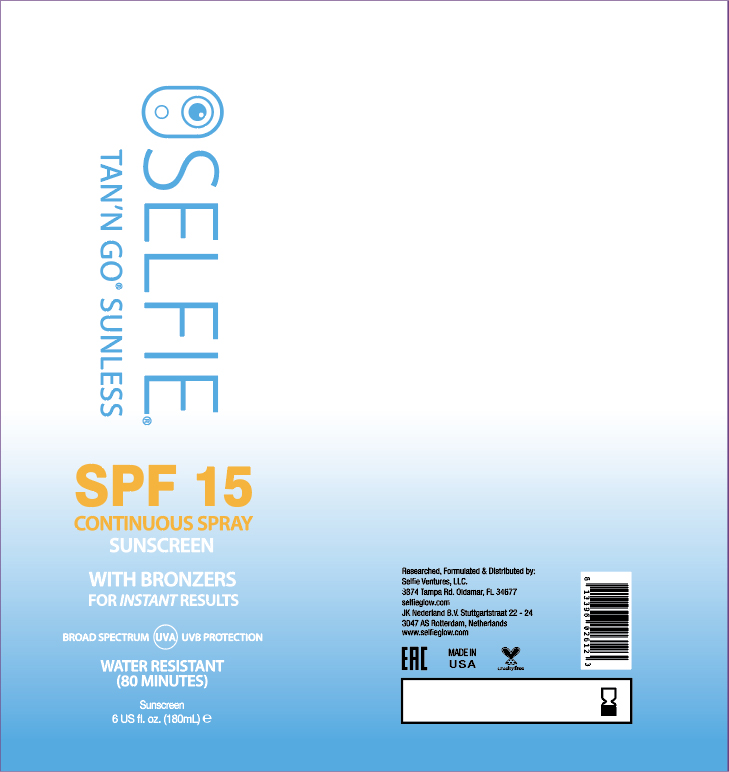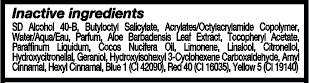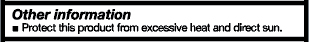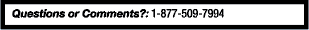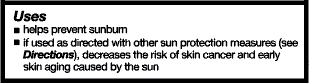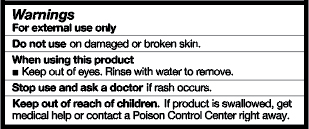 DRUG LABEL: Sunscreen
NDC: 72239-001 | Form: AEROSOL, SPRAY
Manufacturer: OL Products, Inc.
Category: otc | Type: HUMAN OTC DRUG LABEL
Date: 20201231

ACTIVE INGREDIENTS: OCTOCRYLENE 1.85 g/100 g; AVOBENZONE 2 g/100 g; OCTISALATE 5 g/100 g
INACTIVE INGREDIENTS: WATER

SPF 15 SELFIE BOV Continuous Spray